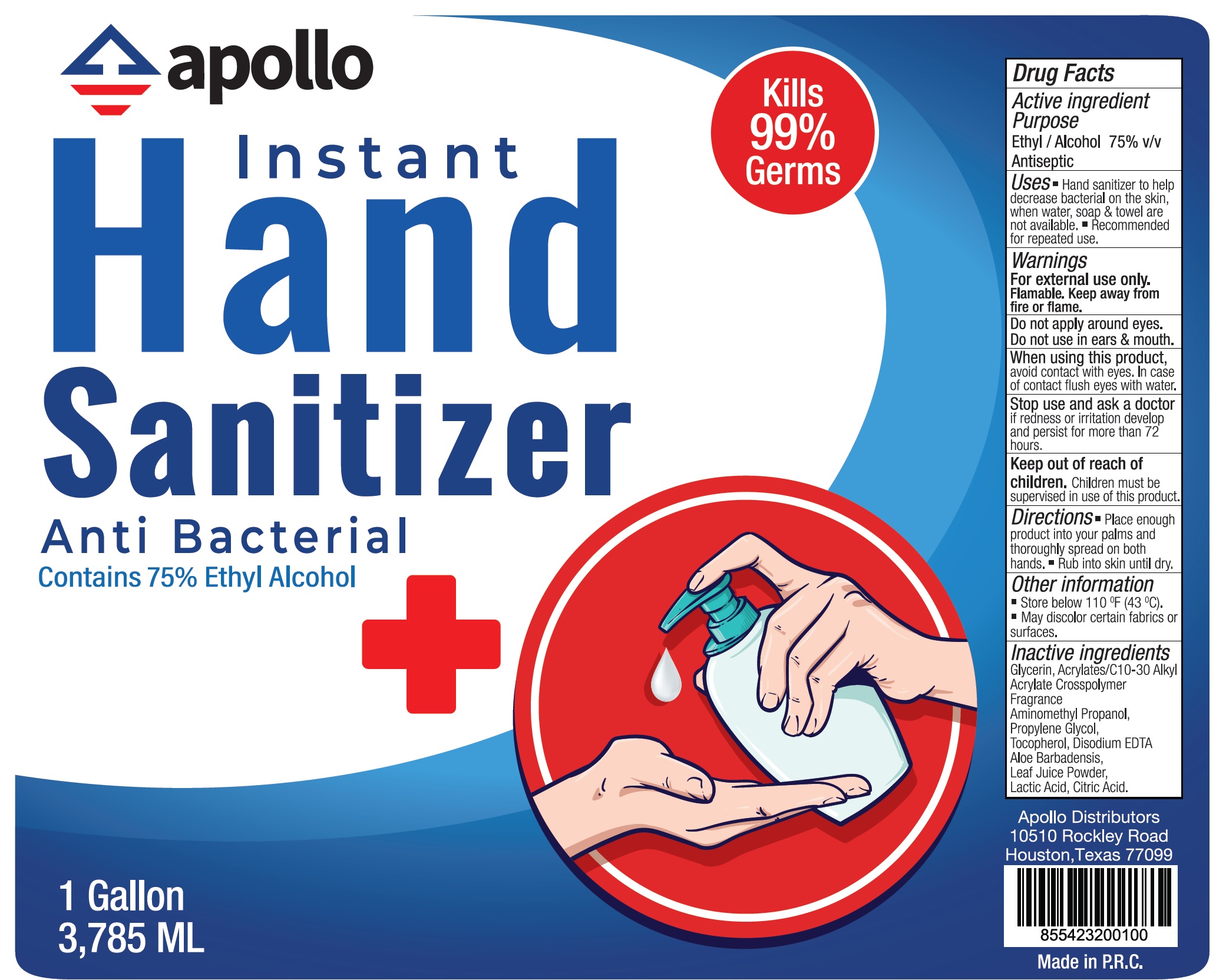 DRUG LABEL: Instant Hand Sanitizer
NDC: 78303-003 | Form: GEL
Manufacturer: SBU GROUP L.P.DBA APOLLO DISTRIBUTORS
Category: otc | Type: HUMAN OTC DRUG LABEL
Date: 20200714

ACTIVE INGREDIENTS: ALCOHOL 0.75 mL/1 mL
INACTIVE INGREDIENTS: GLYCERIN; AMINOMETHYLPROPANOL; ETHYLENE GLYCOL; PROPYLENE GLYCOL; TOCOPHEROL; EDETATE DISODIUM ANHYDROUS; ALOE VERA LEAF; LACTIC ACID, UNSPECIFIED FORM; CITRIC ACID MONOHYDRATE

Instant Hand Sanitizer

Active ingredients

Ethyl / Alcohol 75% v/v

Purpose

Antiseptic

Uses

- Hand sanitizer to help decrease bacterial on the skin, when water, soap & towel are not available.
- Recommended for repeated use.

Warnings

For external use only. Flamable. Keep away from fire or flame.

Do not apply around eyes.

Do not use in ears & mouth.

When using product,

Avoid contact with eyes. In case of contact flush eyes with water.

Stop use and ask a doctor

if redness or irritation develop and persists for more than 72 hours.

Keep out of reach of children.

Children must be supervised in use of htis product.

Directions

- Place enough product into your palms and thoroughly spread on both hands.
- Rub into skin until dry.

Other information

- Store below 110 °F (43 °C).
- May discolor certain fabrics or surfaces.

Inactive ingredients

Glycerin, Acrylates/C 10-30 Alkyl Acrylate Crosspolymer Fragrance Aminomethyl Propanol, Propylene Glycol, Tocopherol, Disodium EDTA, Aloe Barbadensis Leaf Juice Powder, Lactic Acid, Citric acid.